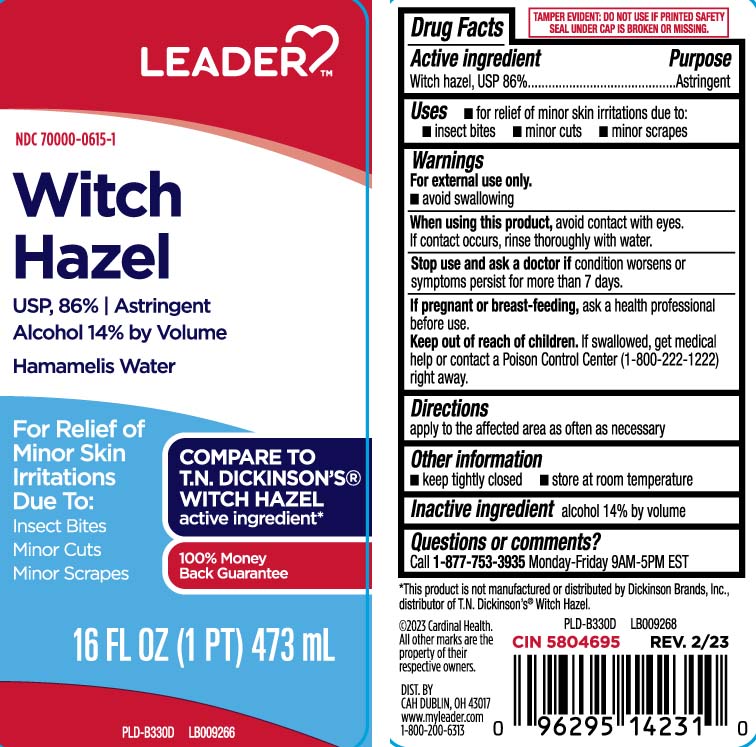 DRUG LABEL: Witch Hazel
NDC: 70000-0615 | Form: LIQUID
Manufacturer: Cardinal Health (Leader) 70000
Category: otc | Type: HUMAN OTC DRUG LABEL
Date: 20250204

ACTIVE INGREDIENTS: WITCH HAZEL 842 mg/1 mL
INACTIVE INGREDIENTS: ALCOHOL

Drug Facts

Active ingredient

Witch hazel, USP 86%

Purpose

Astringent

Uses

- for relief of minor skin irritations due to:
  - insect bites
  - minor cuts
  - minor scrapes

Warnings

For external use only.

- Avoid swallowing.

When using this product

avoid contact with eyes. If contact occurs, rinse thoroughly with water.

Stop use and ask a doctor if

condition worsens or symptoms persist for more than 7 days

If pregnant or breast-feeding,

ask a health professional before use.

Keep out of reach of children.

If swallowed, get medical help or contact a Poison Control Center (1-800-222-1222) right away..

Directions

apply to the affected area as often as necessary.

Other information

- keep tightly closed
- store at room temperature

Inactive ingredient

alcohol 14% by volume

Questions or comments?

Call 1-877-753-3935 Monday-Friday 9AM-5PM EST

Principal Display Panel

COMPARE TOT.N. DICKINSON'S® WITCH HAZEL active ingredient*

Witch Hazel

USP, 86% | Astringent

Alcohol 14% by Volume

Hamamelis Water

For relief of

Minor Skin Irritations

Due To:

Insect Bites

Minor Cuts

Minor Scrapes

FL OZ (mL)

*This product is not manufactured or distributed by Dickinson Brands, Inc., distributor of T.N. Dickinson's Witch Hazel.

TAMPER EVIDENT: DO NOT USE IF PRINTED SAFETY SEAL UNDER CAP IS BROKEN OR MISSING.

DIST. BY

CAH DUBLIN, OH 43017

www.myleader.com

Package Label

LEADER Witch Hazel